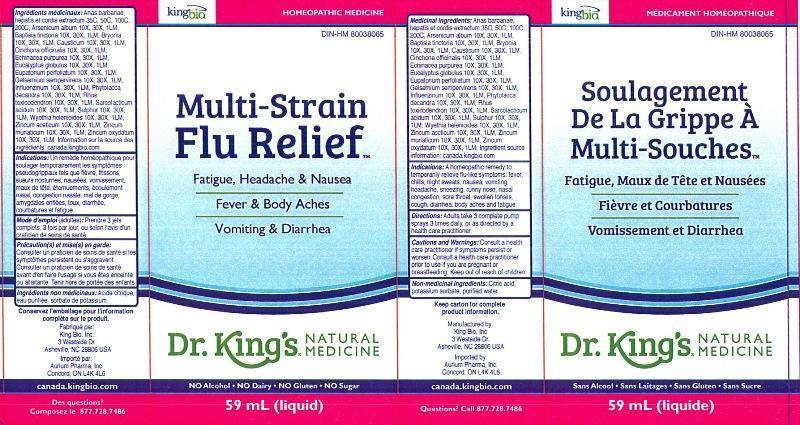 DRUG LABEL: Multi-Strain Flu Relief
NDC: 57955-1801 | Form: LIQUID
Manufacturer: King Bio Inc.
Category: homeopathic | Type: HUMAN OTC DRUG LABEL
Date: 20140822

ACTIVE INGREDIENTS: CAIRINA MOSCHATA HEART/LIVER AUTOLYSATE 35 [hp_C]/59 mL; ARSENIC TRIOXIDE 10 [hp_X]/59 mL; BAPTISIA TINCTORIA ROOT 10 [hp_X]/59 mL; BRYONIA ALBA ROOT 10 [hp_X]/59 mL; CAUSTICUM 10 [hp_X]/59 mL; CINCHONA OFFICINALIS BARK 10 [hp_X]/59 mL; ECHINACEA PURPUREA 10 [hp_X]/59 mL; EUCALYPTUS GLOBULUS LEAF 10 [hp_X]/59 mL; EUPATORIUM PERFOLIATUM FLOWERING TOP 10 [hp_X]/59 mL; GELSEMIUM SEMPERVIRENS ROOT 10 [hp_X]/59 mL; INFLUENZA A VIRUS 10 [hp_X]/59 mL; INFLUENZA B VIRUS 10 [hp_X]/59 mL; PHYTOLACCA AMERICANA ROOT 10 [hp_X]/59 mL; TOXICODENDRON PUBESCENS LEAF 10 [hp_X]/59 mL; LACTIC ACID, L- 10 [hp_X]/59 mL; SULFUR 10 [hp_X]/59 mL; WYETHIA HELENIOIDES ROOT 10 [hp_X]/59 mL; ZINC ACETATE ANHYDROUS 10 [hp_X]/59 mL; ZINC CHLORIDE 10 [hp_X]/59 mL; ZINC OXIDE 10 [hp_X]/59 mL
INACTIVE INGREDIENTS: CITRIC ACID MONOHYDRATE; POTASSIUM SORBATE; WATER

Multi-Strain Flu Relief Soulagement De La Grippe À Multi-Souches

ACTIVE INGREDIENT

Medicinal ingredients/Ingrédients médicinaux: Anas barbariae, hepatis et cordis extractum, 30C, 50C, 100C, 200C, Arsenicum album 10X, 30X, 1LM, Baptisia tinctoria 10X, 30X, 1LM, Bryonia 10X, 30X, 1LM, Causticum 10X, 30X, 1LM. Cinchona officinalis 10X, 30X, 1LM, Echinacea purpurea 10X, 30X,1LM, Eupatorium perfoliatum 10X, 30X 1LM, Gelsemium sempervirens 10X, 30X, 1LM, Influenzinum 10X, 30X, 1LM, Phytolacca decandra 10X, 30X, 1LM, Rhus toxicodendron 10X, 30X,1LM, Sarcolacticum acidum 10X, 30X, 1LM, Sulphur 10X, 30X, 1LM, Wyethia helenioides 10X, 30X, 1LM, Zincum aceticum 10X, 30X, 1LM, Zincum muriaticum 10X, 30X, 1LM, Zincum oxydatum 10X, 30X, 1LM. . Ingredient source information sur la source des ingrédients: canada.kingbio.com

INACTIVE INGREDIENT

Non-medicinal ingredients: Citric acid, potassium sorbate, purified water.

Ingrédients non médicinaux: Acide citrique, eau purifiée, sorbate de potassium.

PURPOSE

Indications: A homeopathic remedy to temporarily relieve flu-like symptoms: fever, chills, night sweats, nausea, vomiting, headache, sneezing, runny nose, nasal congestion, sore throat, swollen tonsils, cough, diarrhea, body aches and fatigue.

Indications: Un remède homéopathique pour soulager temporairement les symptõmes pseudogrippaux tels que fièvre, frissons, sueurs nocturns, nausées, vomissement, maux de tête éternuements, écoulement nasal, congestion nasale, mal de gorge, amygdales enfles, toux, diarrhée, courbatures et fatigue.

DOSAGE AND ADMINISTRATION

Directions: Adults take 3 complete pump sprays 3 times daily, or as directed by a health care practitioner.

Mode d'emploi (adultes): Prendre 3 jets complets, 3 fois par jour, ou selon l'avis d'un praticien de soins de santé.

INDICATIONS AND USAGE

Indications: A homeopathic remedy to temporarily relieve flu-like symptoms:

- fever
- chills
- night sweats
- nausea
- vomiting
- headache
- sneezing
- runny nose
- nasal congestion
- sore throat
- swollen tonsils
- cough
- diarrhea
- body aches
- fatigue

Indications: Un remède homéopathique pour soulager temporairement les symptõmes pseudogrippaux tels que

- fièvre
- frissons
- sueurs nocturns
- nausées
- vomissement
- maux de tête éternuements
- écoulement nasal
- congestion nasale
- mal de gorge
- amygdales enflées
- toux
- diarrhée
- courbatures et fatigue

WARNINGS

Cautions and Warnings: Consult a health care practitioner if symptoms persist or worsen. Consult a health care practitioner prior to use if you are pregnant or breastfeeding.

Précaution(s) et mise(s) en garde: Consulter un praticien de soins de santé si les symptômes persistent ou s'aggravent. Consulter un praticien de soins de santé avant d'en faire l'usage si vous êtes enceinte ou allaitante.

Keep out of reach of children.

Tenir hors de portée des enfants.